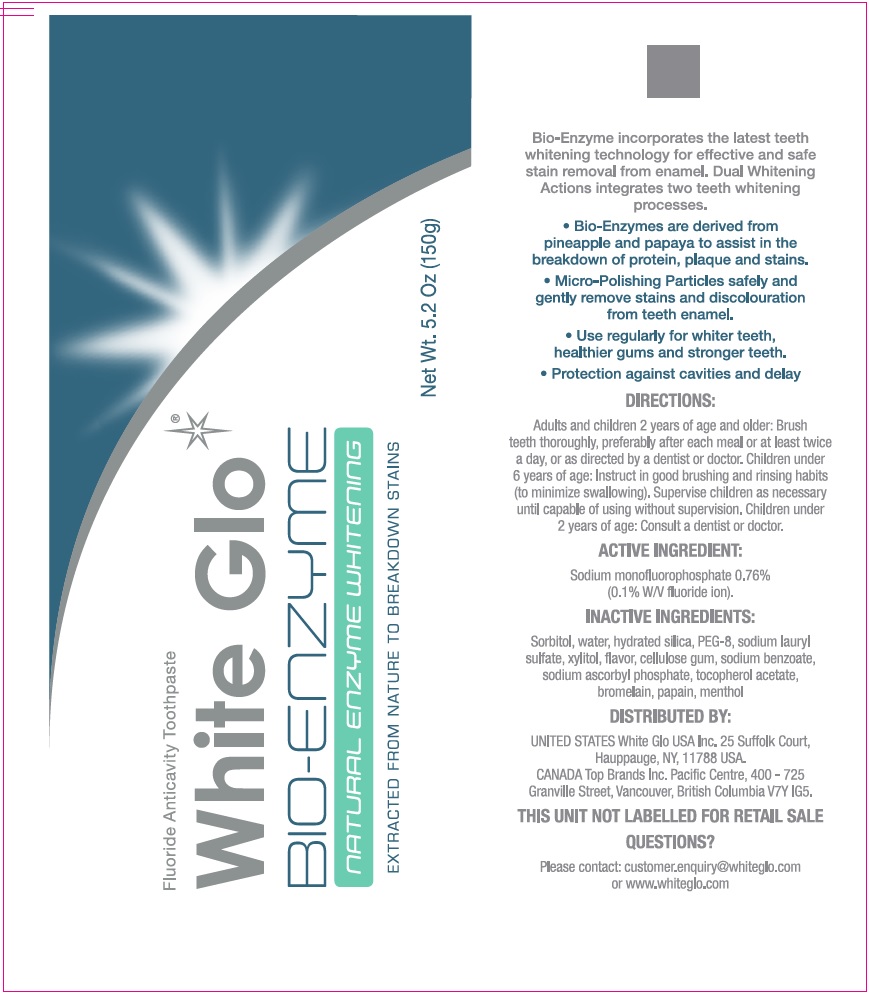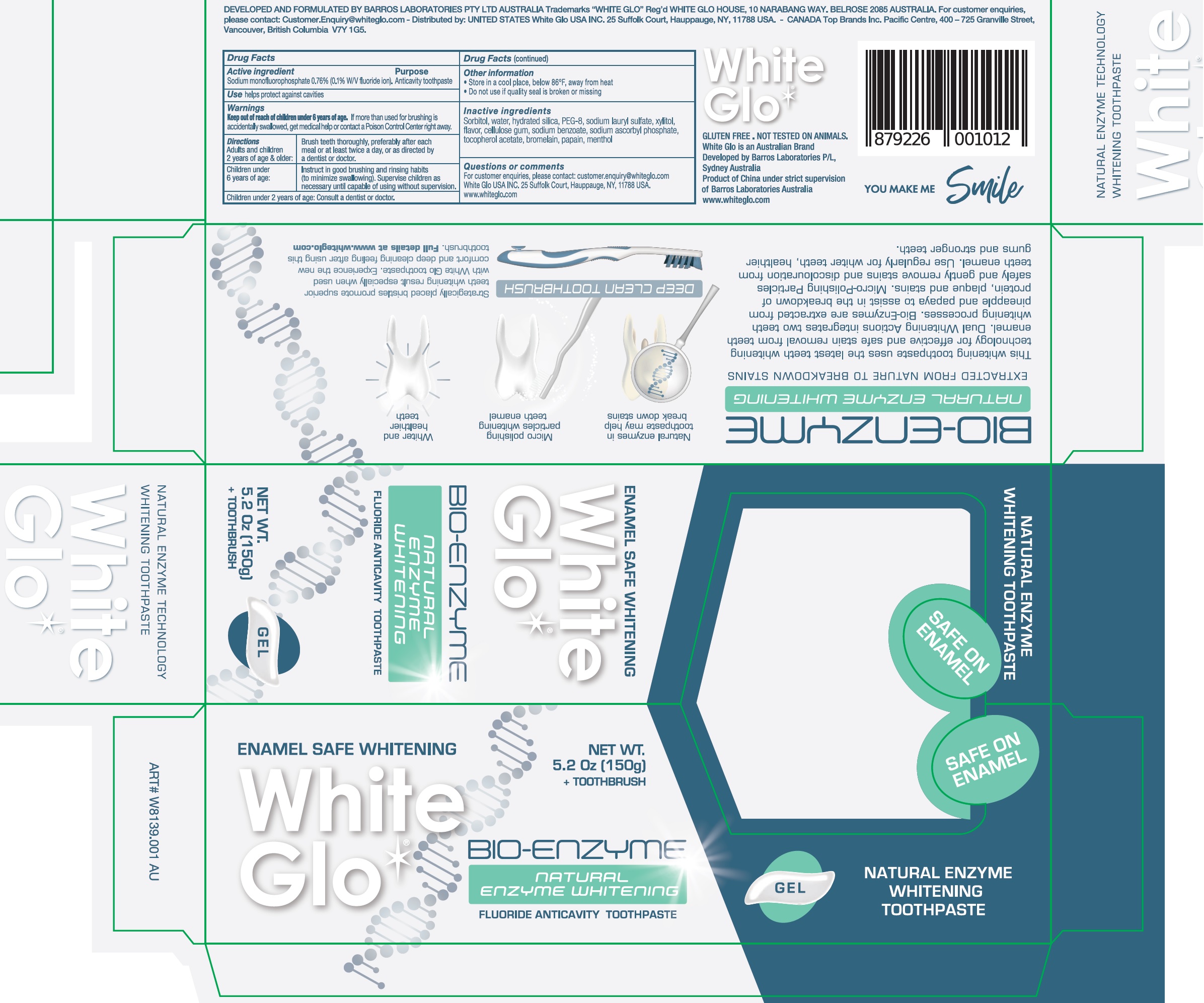 DRUG LABEL: WHITE GLO BIO-ENZYME
NDC: 73656-005 | Form: KIT | Route: DENTAL
Manufacturer: WHITE GLO USA INC
Category: otc | Type: HUMAN OTC DRUG LABEL
Date: 20250226

ACTIVE INGREDIENTS: SODIUM MONOFLUOROPHOSPHATE 7.6 mg/1 g
INACTIVE INGREDIENTS: SORBITOL; WATER; HYDRATED SILICA; POLYETHYLENE GLYCOL 400; SODIUM LAURYL SULFATE; XYLITOL; METHYL SALICYLATE; CARBOXYMETHYLCELLULOSE SODIUM, UNSPECIFIED FORM; SODIUM BENZOATE; SODIUM ASCORBYL PHOSPHATE; .ALPHA.-TOCOPHEROL ACETATE; BROMELAINS; PAPAIN; MENTHOL

WHITE GLO BIO-ENZYME Kit

Active ingredient

Sodium monofluorophosphate 0.76% (0.1% W/V fluoride ion)

Purpose

Anticavity toothpaste

Use

helps protect against cavities

Warnings

Keep out of reach of children under 6 years of age.

If more than used for brushing is accidentally swallowed, get medical help or contact a Poison Control Center right away.

Directions

Adults and children 2 years of age & older: | Brush teeth thoroughly, preferably after each meal or at least twice a day, or as directed by a dentist or doctor.
Children under 6 years of age: | Instruct in good brushing and rinsing habits (to minimize swallowing). Supervise children as necessary until capable of using without supervision.

Consult a dentist or doctor. Children under 2 years of age:

Other information

- Store in a cool place, below 86°F, away from heat
- Do not use if quality seal is broken or missing

Inactive ingredients

sorbitol, water, hydrated silica, PEG-8, sodium lauryl sulfate, xylitol, flavor, cellulose gum, sodium benzoate, sodium ascorbyl phosphate, tocopherol acetate, bromelain, papain, menthol

Questions or comments

For customer enquiries, please contact: customer.enquiry@whiteglo.com White Glo USA INC.25 Suffolk Court, Hauppauge, NY, 11788 USA. www.whiteglo.com